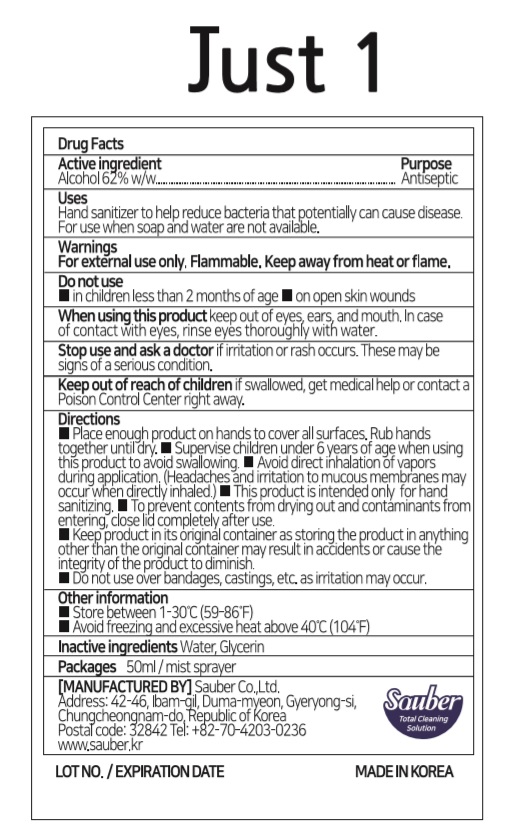 DRUG LABEL: Just 1
NDC: 78880-562 | Form: SPRAY
Manufacturer: Sauber Co.,Ltd.
Category: otc | Type: HUMAN OTC DRUG LABEL
Date: 20200710

ACTIVE INGREDIENTS: ALCOHOL 31 mL/50 mL
INACTIVE INGREDIENTS: GLYCERIN; WATER

Just 1 | 50 ml | Mist sprayer